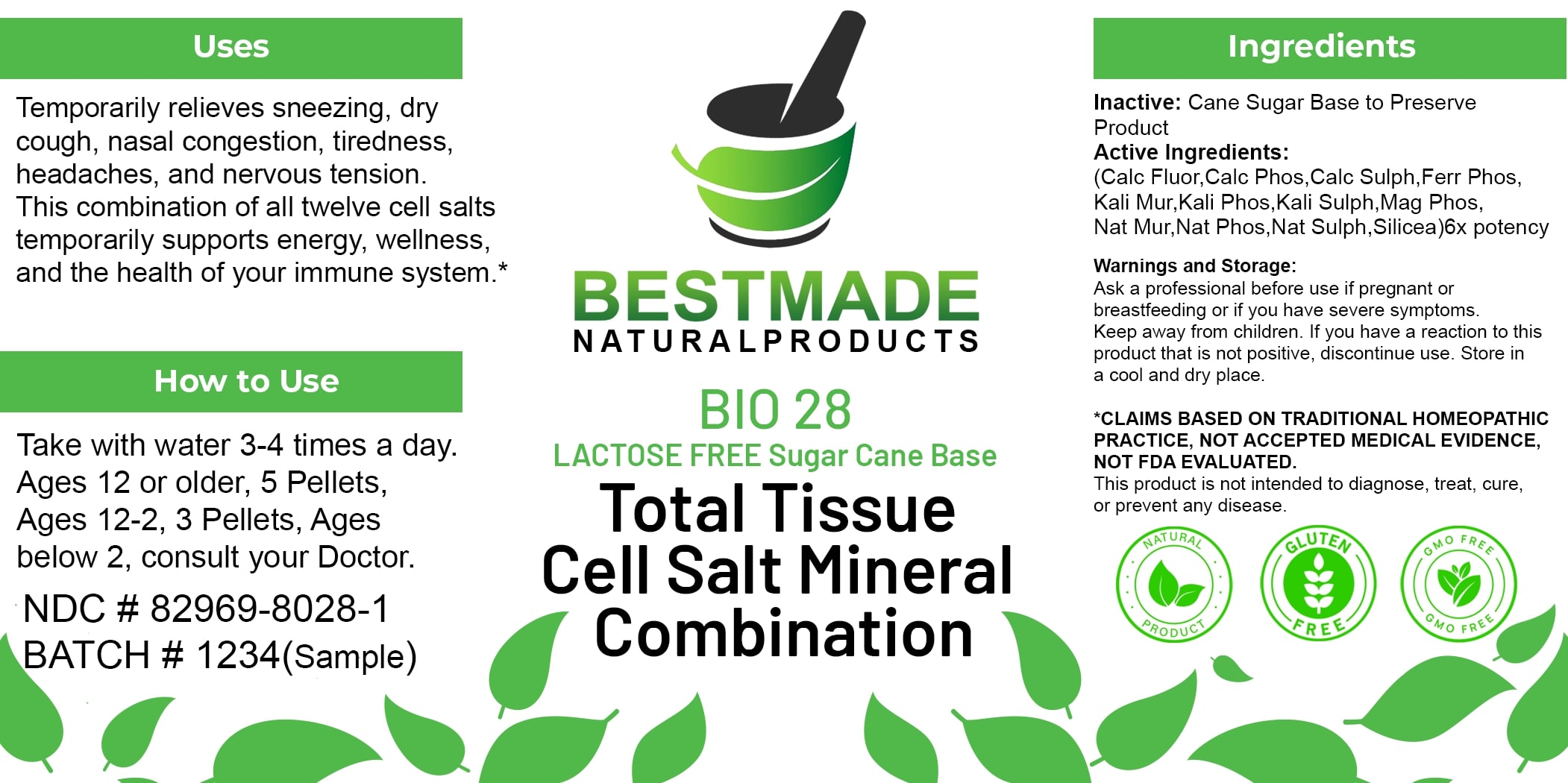 DRUG LABEL: Bestmade Natural Products BIO28 Lactose Free
NDC: 82969-8028 | Form: TABLET, SOLUBLE
Manufacturer: Bestmade Natural Products
Category: homeopathic | Type: HUMAN OTC DRUG LABEL
Date: 20250313

ACTIVE INGREDIENTS: SILICA 6 [hp_X]/6 [hp_X]; FERROSOFERRIC PHOSPHATE 6 [hp_X]/6 [hp_X]; DIBASIC POTASSIUM PHOSPHATE 6 [hp_X]/6 [hp_X]; POTASSIUM SULFATE 6 [hp_X]/6 [hp_X]; MAGNESIUM PHOSPHATE, DIBASIC TRIHYDRATE 6 [hp_X]/6 [hp_X]; SODIUM PHOSPHATE, DIBASIC, HEPTAHYDRATE 6 [hp_X]/6 [hp_X]; SODIUM SULFATE 6 [hp_X]/6 [hp_X]; CALCIUM SULFATE ANHYDROUS 6 [hp_X]/6 [hp_X]; POTASSIUM CHLORIDE 6 [hp_X]/6 [hp_X]; SODIUM CHLORIDE 6 [hp_X]/6 [hp_X]; CALCIUM FLUORIDE 6 [hp_X]/6 [hp_X]; TRIBASIC CALCIUM PHOSPHATE 6 [hp_X]/6 [hp_X]
INACTIVE INGREDIENTS: SUCROSE 6 [hp_X]/6 [hp_X]

BIO28 Total Tissue Cell Salt Mineral Combination LACTOSE FREE Sugar Cane Base

DOSAGE AND ADMINISTRATION

How to Use

Take with water 3-4 times a day. Ages 12 or older, 5 Pellets, Ages 12-2, 3 Pellets, Ages below 2, consult your Doctor.

Inactive:

Cane Sugar Base to Preserve Product

Active Ingredients:
(Calc Fluor, Calc Phos, Calc Sulph, Ferr Phos, Kali Mur, Kali Phos, Kali Sulph, Mag Phos, Nat Mur, Nat Phos, Nat Sulph, Silicea) 6x potency

Uses

Temporarily relieves sneezing, dry cough, nasal congestion, tiredness, headaches, and nervous tension. This combination of all twelve cell salts temporarily supports energy, wellness, and the health of your immune system.*

*CLAIMS BASED ON TRADITIONAL HOMEOPATHIC PRACTICE, NOT ACCEPTED MEDICAL EVIDENCE, NOT FDA EVALUATED.

This product is not intended to diagnose, treat, cure, or prevent any disease.

Uses

Temporarily relieves sneezing, dry cough, nasal congestion, tiredness, headaches, and nervous tension. This combination of all twelve cell salts temporarily supports energy, wellness, and the health of your immune system.*

*CLAIMS BASED ON TRADITIONAL HOMEOPATHIC PRACTICE, NOT ACCEPTED MEDICAL EVIDENCE, NOT FDA EVALUATED.

This product is not intended to diagnose, treat, cure, or prevent any disease.

KEEP OUT OF REACH OF CHILDREN

Warnings and Storage:

Ask a professional before use if pregnant or breastfeeding or if you have severe symptoms. Keep away from children. If you have a reaction to this product that is not positive, discontinue use. Store in a cool and dry place.

Warnings and Storage:

Ask a professional before use if pregnant or breastfeeding or if you have severe symptoms. Keep away from children. If you have a reaction to this product that is not positive, discontinue use. Store in a cool and dry place.

*CLAIMS BASED ON TRADITIONAL HOMEOPATHIC PRACTICE, NOT ACCEPTED MEDICAL EVIDENCE NOT FDA EVALUATED.

This product is not intended to diagnose, treat, cure, or prevent any disease.

Entire package label